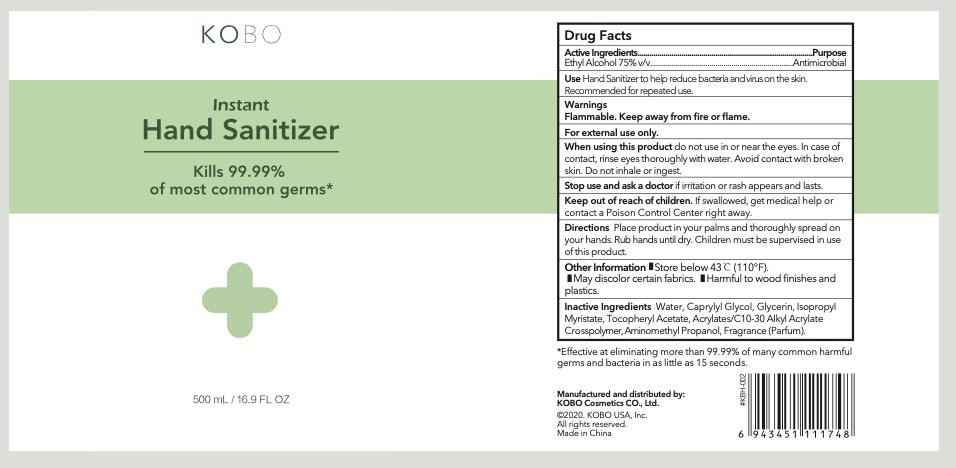 DRUG LABEL: KOBOInstant Hand Sanitizer
NDC: 42001-001 | Form: LIQUID
Manufacturer: KOBO Cosmetics Co., Ltd.
Category: otc | Type: HUMAN OTC DRUG LABEL
Date: 20200421

ACTIVE INGREDIENTS: ALCOHOL 375 mL/500 mL
INACTIVE INGREDIENTS: CARBOMER COPOLYMER TYPE A (ALLYL PENTAERYTHRITOL CROSSLINKED); .ALPHA.-TOCOPHEROL ACETATE; WATER; CAPRYLYL GLYCOL; ISOPROPYL MYRISTATE; FRAGRANCE LAVENDER & CHIA F-153480; GLYCERIN; AMINOMETHYLPROPANOL

DOSAGE AND ADMINISTRATION

Keep away from fire or flame.

INACTIVE INGREDIENT

Water,

Caprylyl Glycol,

Glycerin, Isopropyl Myristate,

Tocopheryl Acetate,

Acrylates/C10-30 Alkyl Acrylate Crosspolymer

Aminomethyl Propanol

Fragrance (Parfum).

INDICATIONS AND USAGE

Place productin your palms and thoroughly spread on your hands. Rub hands until dry. Children must be supervised in use of this product.

ACTIVE INGREDIENT

Ethyl Alcohol

keep out of children

PURPOSE

Disinfection
Sterilization
No Rinseing

When using this product do not use in or near the eyes. In case of contact, rinse eyes thoroughly with water. Awoid contact with broken
skin. Do not inhale or ingest.Stop use and ask a doctor if iritation or rash appears and lasts.Keep out of reach of children. If swallowed, get medical help or contact a Poison Control Center right away.